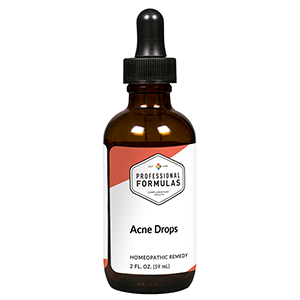 DRUG LABEL: Acne Drops
NDC: 63083-2001 | Form: LIQUID
Manufacturer: Professional Complementary Health Formulas
Category: homeopathic | Type: HUMAN OTC DRUG LABEL
Date: 20190815

ACTIVE INGREDIENTS: ARCTIUM LAPPA ROOT OIL 3 [hp_X]/59 mL; BERBERIS AQUIFOLIUM ROOT BARK 3 [hp_X]/59 mL; CENTELLA ASIATICA LEAF 3 [hp_X]/59 mL; RHODODENDRON TOMENTOSUM LEAFY TWIG 4 [hp_X]/59 mL; STRYCHNOS NUX-VOMICA SEED 6 [hp_X]/59 mL; SANGUINARIA CANADENSIS ROOT 6 [hp_X]/59 mL; SILICON DIOXIDE 6 [hp_X]/59 mL; SULFUR 6 [hp_X]/59 mL; ANTIMONY TRISULFIDE 8 [hp_X]/59 mL; POTASSIUM BROMIDE 12 [hp_X]/59 mL; SODIUM CHLORIDE 12 [hp_X]/59 mL; CARBO ANIMALIS 15 [hp_X]/59 mL
INACTIVE INGREDIENTS: ALCOHOL; WATER

C1

ACTIVE INGREDIENTS

Arctium lappa 3X
Berberis aquifolium 3X
Hydrocotyle asiatica 3X
Ledum palustre 4X
Nux vomica 6X
Sanguinaria canadensis 6X
Silicea 6X
Sulphur 6X
Antimonium crudum 8X
Kali bromatum 12X
Natrum muriaticum 12X
Carbo animalis 15X

QUESTIONS

Professional Formulas

PO Box 2034 Lake Oswego, OR 97035

INDICATIONS

For the temporary relief of minor acne-like conditions, blackheads, or pimples.*

PURPOSE

*Claims based on traditional homeopathic practice, not accepted medical evidence. Not FDA evaluated.

WARNINGS

If symptoms do not improve, are severe, or are accompanied by scarring, consult a doctor. Keep out of the reach of children. In case of overdose, get medical help or contact a poison control center right away. If pregnant or breastfeeding, ask a healthcare professional before use.

Keep out of the reach of children.

PREGNANCY OR BREAST FEEDING

If pregnant or breastfeeding, ask a healthcare professional before use.

DIRECTIONS

Place drops under tongue 30 minutes before/after meals. Adults and children 12 years and over: Take 10 drops up to 3 times per day. Consult a physician for use in children under 12 years of age.

OTHER INFORMATION

Tamper resistant. If seal is broken, do not use. After opening, close container tightly and store at room temperature away from heat.

INACTIVE INGREDIENTS

20% ethanol, purified water.

LABEL

Est 1985

Professional Formulas

Complementary Health

Acne Drops

Homeopathic Remedy

2 FL. OZ. (59 mL)